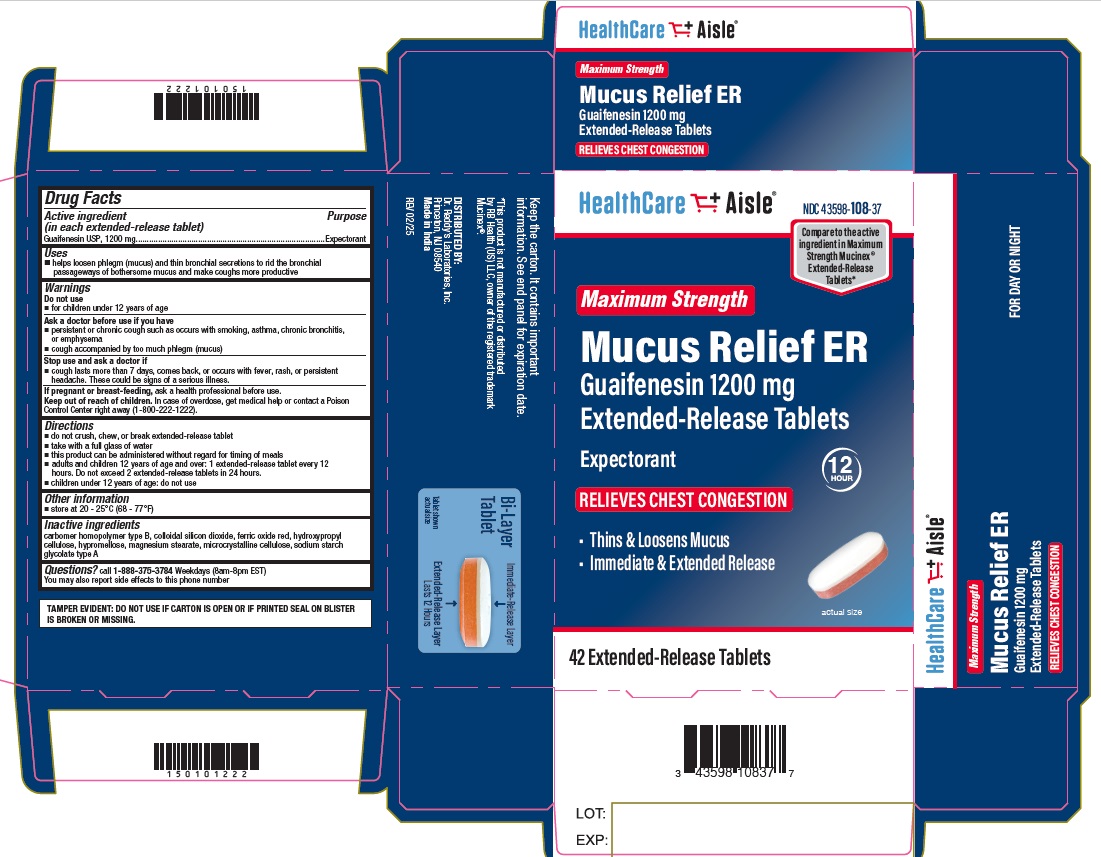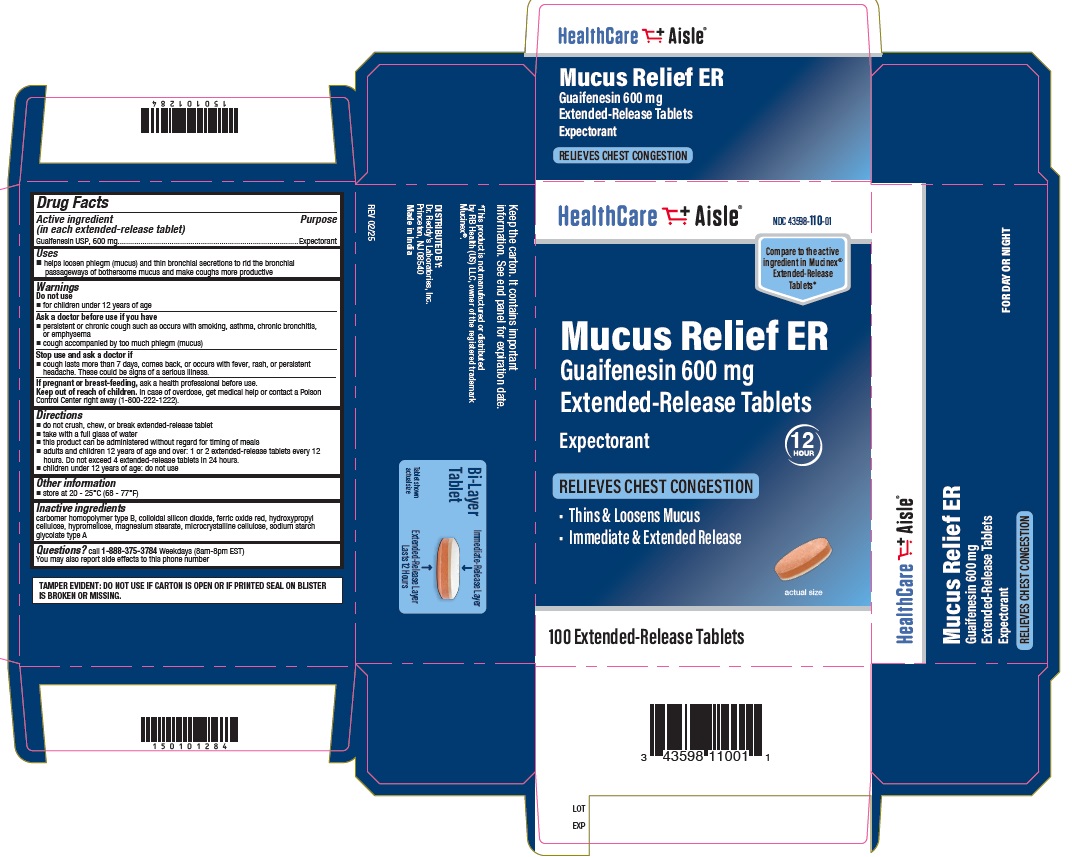 DRUG LABEL: Guaifenesin 600 mg
NDC: 43598-110 | Form: TABLET, EXTENDED RELEASE
Manufacturer: Dr. Reddy's Laboratories Inc.
Category: otc | Type: HUMAN OTC DRUG LABEL
Date: 20250922

ACTIVE INGREDIENTS: Guaifenesin 600 mg/1 1
INACTIVE INGREDIENTS: Carbomer Homopolymer Type B (Allyl Pentaerythritol Crosslinked); Silicon Dioxide; Ferric Oxide Red; Hydroxypropyl Cellulose (110000 Wamw); Hypromellose 2910 (10000 Mpa.S); Hypromellose 2208 (4000 Mpa.S); Magnesium Stearate; Microcrystalline Cellulose; Sodium Starch Glycolate Type A Potato

Drug Facts

Active ingredient(s)

Guaifenesin 600 mg (for 600mg)

Guaifenesin 1200 mg (for 1200 mg)

Purpose

Expectorant

Use(s)

- helps loosen phlegum (mucus) and thin bronchial secretions to rid the bronchial passageways of bothersome mucus and make coughs more productive

Warnings

Applicable warning(s) in 201.66(c)(5)(i) and (ii)

Do not use

- For children under 12 years age

Ask a doctor before use if

- persistent or chronic cough such as occurs with smoking, asthma, chronic bronchitis, or emphysema
- cough accompanied by too much phlegm (mucus)

Stop use and ask doctor if

- cough lasts more than 7 days, comes back, or occurs with fever, rash, or persistent headache. These could be signs of a serious illness.

If Pregnancy/Breastfeeding,

ask a health professional before use.

Keep out of reach of children

In case of overdose, get medical help or contact aPoison Control Center right away (1-800-222-1222).

Directions

- do not crush, chew, or break tablet
- take with a full glass of water
- this product can be administered without regard for the timing of meals
- adults and children 12 years of age and over: 1or 2 extended-release tablets every 12 hours. Do not exceed 4 extended-release tablets in 24 hours (for 600 mg)
- adults and children 12 years of age and over: 1 extended-release tablet every 12 hours. Do not exceed 2 extended-release tablets in 24 hours (for 1200 mg)
- children under 12 years of age: do not use

Other information

- store at 20-25°C (68-77°F)

Inactive ingredients

carbomer homopolymer type B, colloidal silicon dioxide, ferric oxide red, hydroxypropyl cellulose, hypromellose, magnesium stearate, microcrystalline cellulose, sodium starch glycolate type A

Questions?

call 1-888-375-3784 Weekdays (8am - 8pm EST)

You may also report side effects to this phone number.

Distributed by:

Dr. Reddy’s Laboratories, Inc.

Princeton, NJ 08540

Made in India

I 0721

Principal Display Panel- 600mg Carton

Guaifenesin Extended-Release Tablets 600 mg Carton Label

Principal Display Panel - 1200 mg Carton

Guaifenesin Extended-Release Tablets 1200 mg Carton Label